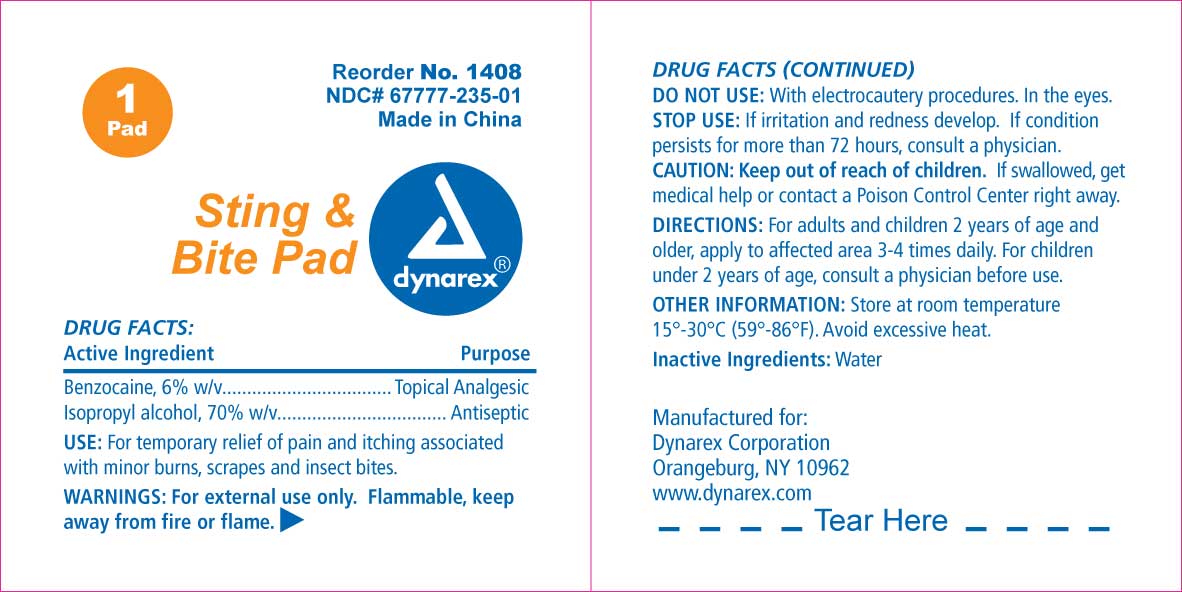 DRUG LABEL: Benzocaine
NDC: 67777-235 | Form: SWAB
Manufacturer: Dynarex Corporation
Category: otc | Type: HUMAN OTC DRUG LABEL
Date: 20110322

ACTIVE INGREDIENTS: BENZOCAINE 0.12 mL/1 1
INACTIVE INGREDIENTS: ISOPROPYL ALCOHOL; WATER

Benzocaine Sting & Bite Pad

Active Ingredient

Active Ingredient Purpose

Benzocaine, 6% w/v Topical Analgesic

Isopropyl Alcohol, 70% w/v Antiseptic

Purpose

- For temporary relief of pain and itching associated with minor burns, scrapes and insect bites.

Keep Out of Reach of Children

- If swallowed, get medical help or contact a Poison Control Center.

Indications and Usage

- For temporary relief of pain and itching associated with minor burns, scrapes and insect bites.

Warnings

- For external use only.
- Flammable, keep away from fire or flame.

Dosage

Directions:

- Adults and children 2 years of age and older, apply to affected area 3-4 times daily.
- Children under 2 years; consult a physician.

Inactive Ingredients

- Inactive Ingredient: Water.

Do Not Use

- With electrocautery procedures.
- In the eyes.

Stop Use

- If irritation and redness develop.
- If condition persists for more than 72 hours, consult a physician.

Storage and Handling

- Avoid excessive heat.
- Store at room temperature: 15 - 30 degrees C (59 - 86 degrees F)

Principal Display

Sting and Bite Pad